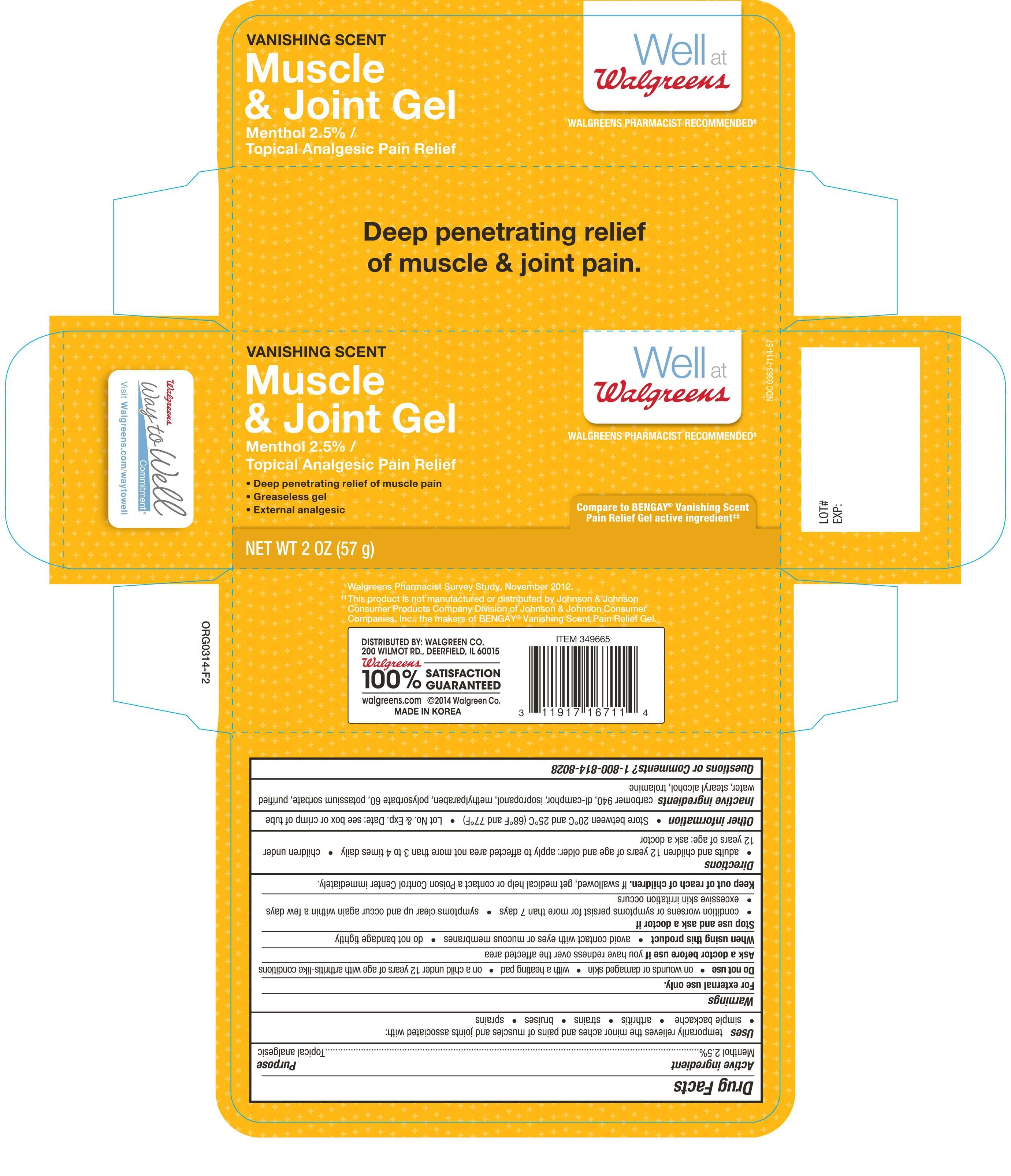 DRUG LABEL: Walgreen Vanishing Scent Muscle and Joint
NDC: 0363-6711 | Form: GEL
Manufacturer: Walgreen Company
Category: otc | Type: HUMAN OTC DRUG LABEL
Date: 20140529

ACTIVE INGREDIENTS: MENTHOL 2.5 g/100 g
INACTIVE INGREDIENTS: CARBOMER 940; CAMPHOR (NATURAL); ISOPROPYL ALCOHOL; METHYLPARABEN; POLYSORBATE 60; POTASSIUM SORBATE; WATER; STEARYL ALCOHOL; TROLAMINE

Active Ingredient Purpose

Menthol 2.5%------------------------------------------------------------------------- Topical analgesic

PURPOSE

Uses temporarily relieves the minor aches and pains of muscles and joints associated with:

- simple backache
- arthritis
- strains
- bruises
- sprains

WARNINGS

For external use only.

DO NOT USE

- on wounds or damaged skin
- with a heating pad
- on a child under 12 years of age with arthritis-like conditions

Ask a doctor before use if you have redness over the affected area

When using this product

- avoid contact with eyes or mucous membranes
- do not bandage tightly

Stop use and ask a doctor if

- condition worsens or symptoms persist for more than 7 days
- symptoms clear up and occur again within a few days
- excessive skin irritation occurs

keep out of reach of children. If swallowed, get medical help or contact a Poison Control Center immediately.

INDICATIONS AND USAGE

- adults and children 12 years of age and older:apply to affected area not more than 3 to 4 times daily
- children under 12 years of age:ask a doctor

STORAGE AND HANDLING

- Store between 20° C and 25° C (68°F and 77°F)
- Lot No. & Exp. Date;see box or crimp of tube

INACTIVE INGREDIENT

carbomer 940, di-camphor, isopropanol, methylparaben, polysorbate 60, potassium sorbate, purified water, stearyl alcohol, trolamine

Questions or Comments? 1-800-814-8028

DOSAGE AND ADMINISTRATION

Distributed By:

Walgreen Co.

200 Wilmot Rd.

Deerfield, IL 60015 USA